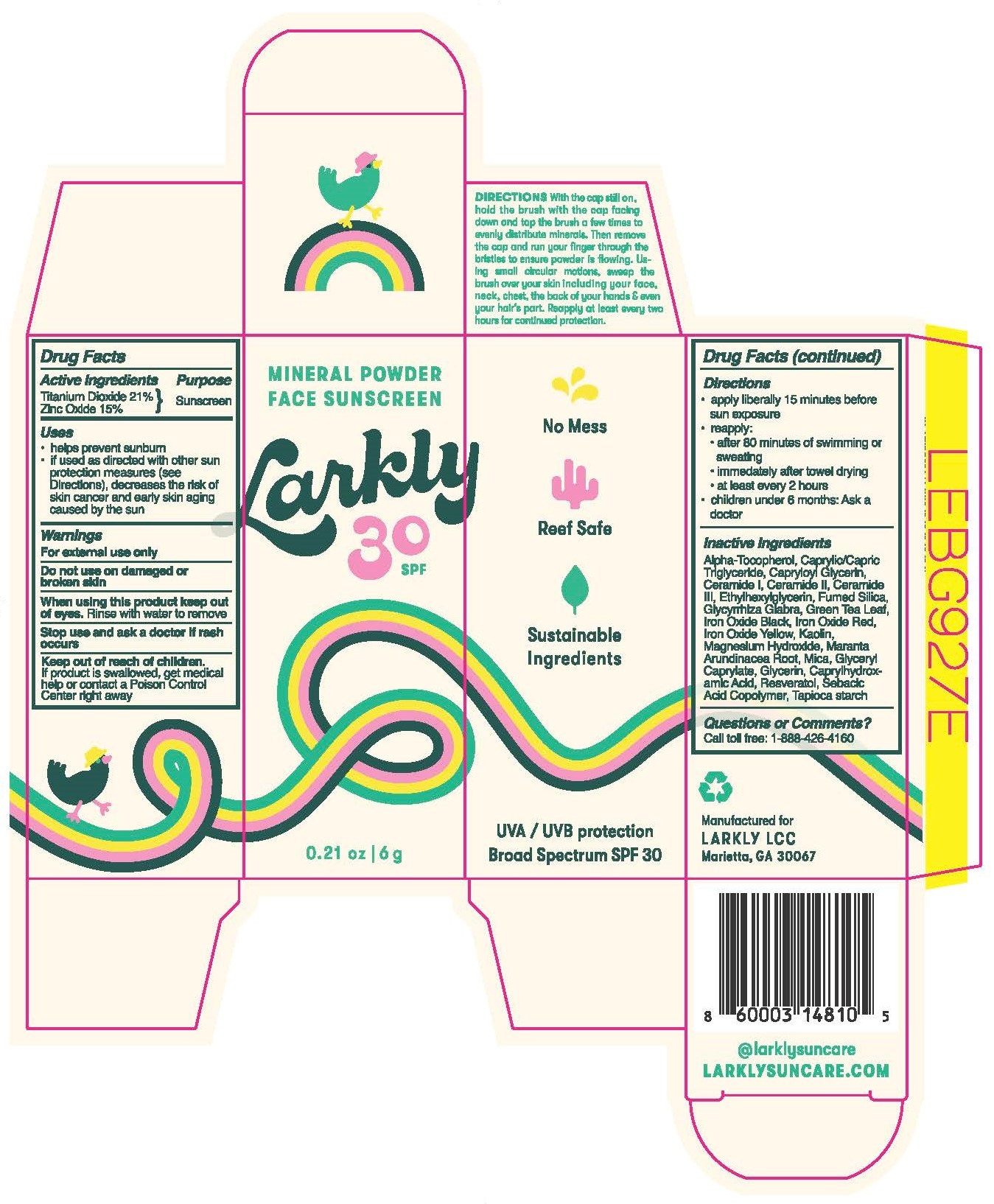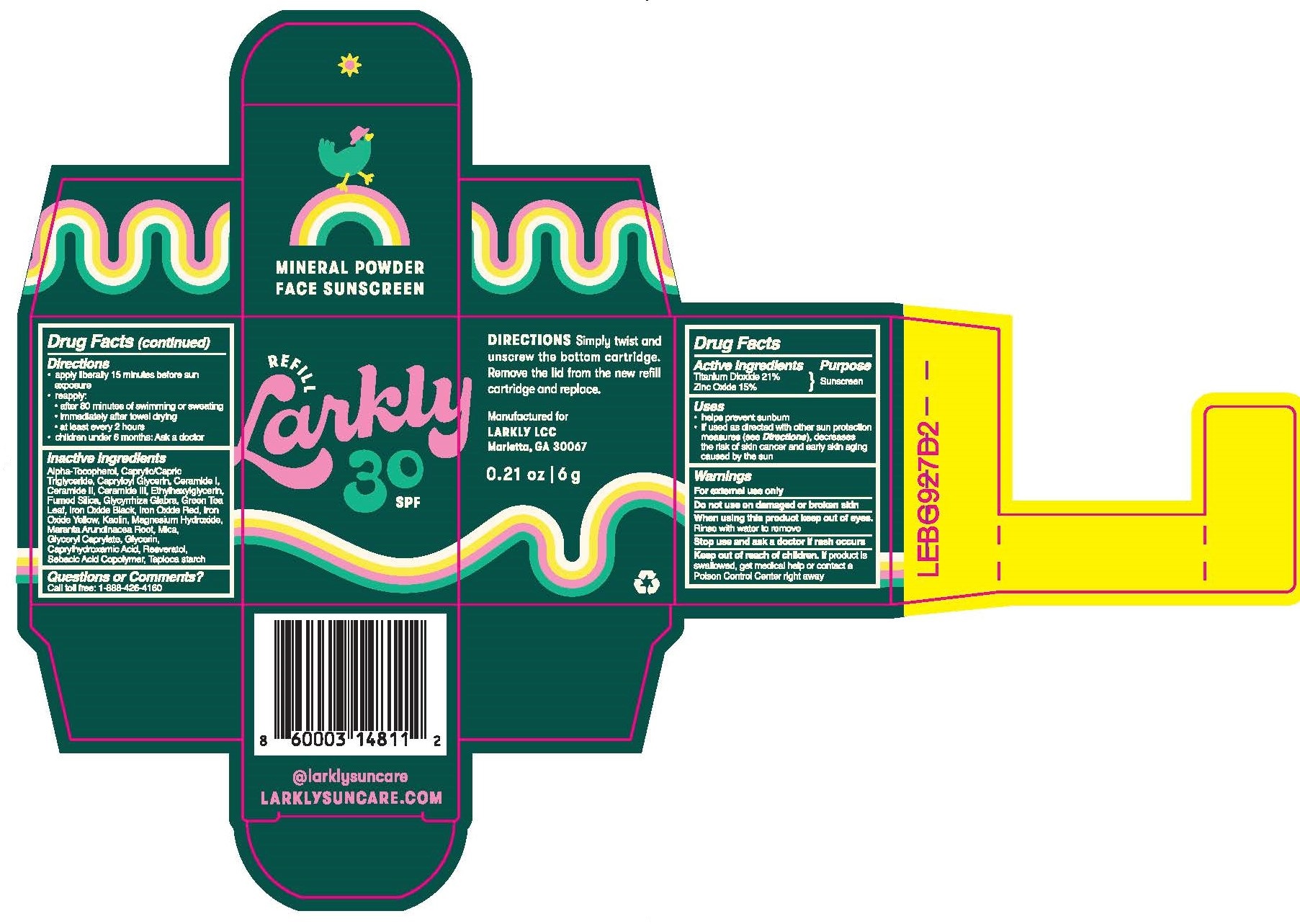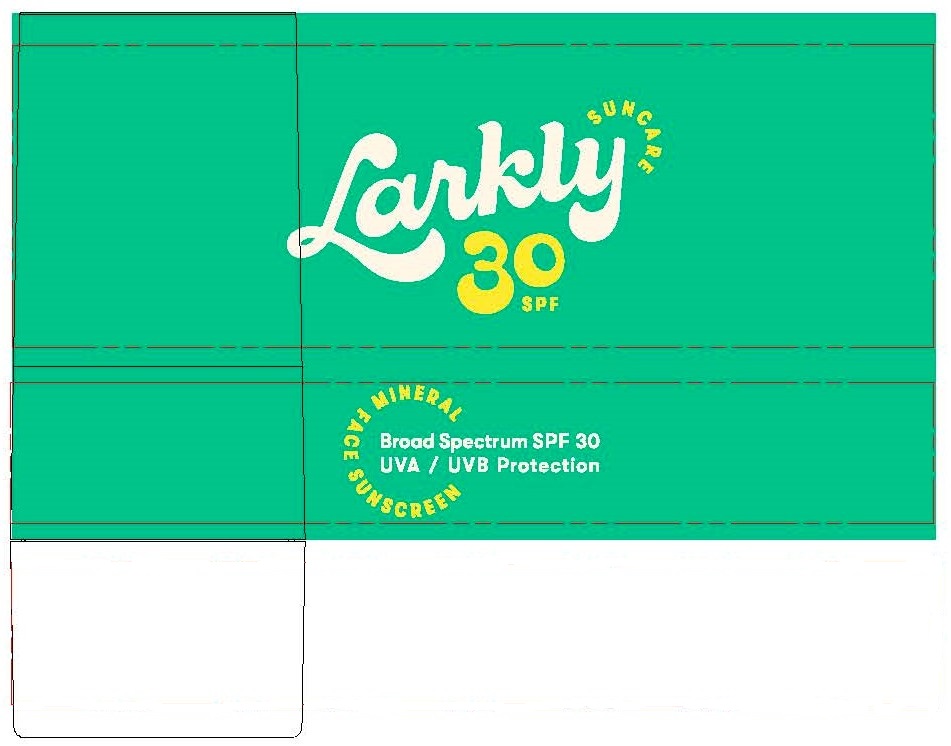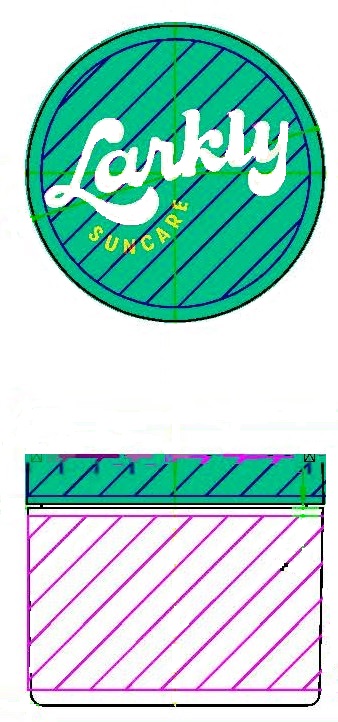 DRUG LABEL: Larkly SPF30 Mineral Powder Face Sunscreen
NDC: 79287-0000 | Form: POWDER
Manufacturer: LARKLY, LLC
Category: otc | Type: HUMAN OTC DRUG LABEL
Date: 20230111

ACTIVE INGREDIENTS: TITANIUM DIOXIDE 0.212 kg/1 kg; ZINC OXIDE 0.15 kg/1 kg
INACTIVE INGREDIENTS: .ALPHA.-TOCOPHEROL, D-; MEDIUM-CHAIN TRIGLYCERIDES; CAPRYLOYL GLYCERIN/SEBACIC ACID COPOLYMER (2000 MPA.S); CERAMIDE 1; CERAMIDE 2; CERAMIDE 3; ETHYLHEXYLGLYCERIN; SILICON DIOXIDE; HEXAMETHYLDISILAZANE; GLYCYRRHIZA GLABRA; GREEN TEA LEAF; FERROSOFERRIC OXIDE; FERRIC OXIDE RED; FERRIC OXIDE YELLOW; KAOLIN; MAGNESIUM HYDROXIDE; MARANTA ARUNDINACEA ROOT; MICA; GLYCERYL CAPRYLATE; GLYCERIN; CAPRYLHYDROXAMIC ACID; RESVERATROL; STARCH, TAPIOCA

Drug Facts

Active Ingredient...........................Purpose

Titanium Dioxide 21.00%..................Sunscreen

Zinc Oxide 15.00%..........................Sunscreen

Uses

- helps prevent sunburn
- if used as directed with other sun protection measures (see Directions), decreases the risk of skin cancer and early aging caused by the sun

Warnings

For external use only

Do not use on damaged or borken skin

When using this product keep out of eyes. Rinse with water to remove

Stop use and ask a doctor if rash occurs

Keep out of reach of children.

If product is swallowed, get medical help or contact a Poison Control Center right away

Directions

- apply liberally 15 minutes before sun exposure
- reapply:
- after 80 minutes of swimming or sweating
- immediately after towel drying
- at least every 2 hours
- children under 6 months: Ask a doctor

Inactive Ingredients

Alpha-Tocopherol, Caprylic/Capric Triglyceride, Capryloyl Glycerin, Ceramide I, Ceramide II, Ceramide III, Ethylhexylglycerin, Fumed Silica, Glycyrrhiza Glabra, Green Tea Leaf, Iron Oxide Black, Iron Oxide Red, Iron Oxide Yellow, Kaolin, Magnesium Hydroxide, Maranta Arundinacea Root, Mica, Glyceryl Caprylate, Glycerin, Caprylhydroxamic Acid, Resveratol, Sebacic Acid Copolymer, Tapioca Starch

Questions or Comments?

Call toll free: 1-888-426-4160